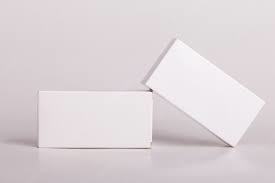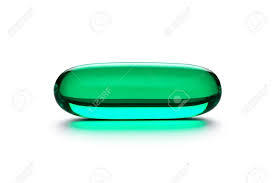 DRUG LABEL: Truemed Group LLC
NDC: 82922-026 | Form: CAPSULE
Manufacturer: Truemed Group LLC
Category: prescription | Type: HUMAN PRESCRIPTION DRUG LABEL
Date: 20220810

ACTIVE INGREDIENTS: CELECOXIB N-DES(BENZENESULFONAMIDE) 200 mg/1 1

CELECOXIB